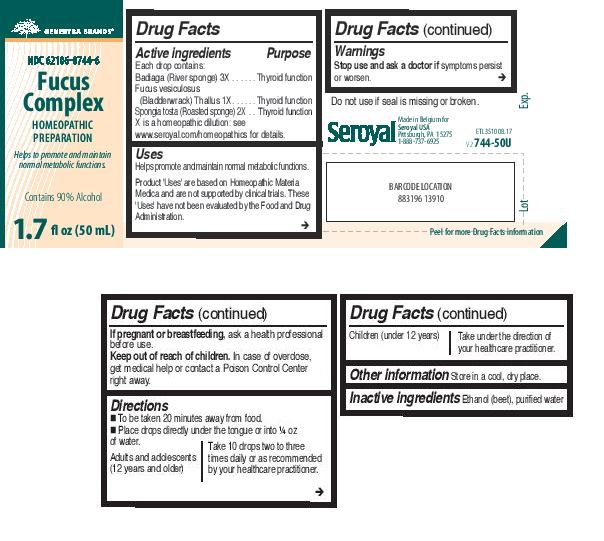 DRUG LABEL: Fucus Complex
NDC: 62106-0744 | Form: LIQUID
Manufacturer: Seroyal USA
Category: homeopathic | Type: HUMAN OTC DRUG LABEL
Date: 20231010

ACTIVE INGREDIENTS: SPONGIA OFFICINALIS SKELETON, ROASTED 2 [hp_X]/50 mL; SPONGILLA LACUSTRIS 3 [hp_X]/50 mL; FUCUS VESICULOSUS 1 [hp_X]/50 mL
INACTIVE INGREDIENTS: WATER; ALCOHOL

Fucus Complex

ACTIVE INGREDIENT

Each drop contains equal parts of:

Fucus vesiculosus (Bladder wrack) 1X

Spongia tosta (Roasted sponge) 2X

Badiaga (Fresh water sponge) 3X

PURPOSE

Indications

Helps promote and maintain normal metabolic functions.

Warnings
If pregnant or breastfeeding, ask a health professional before use.
Keep out of reach of children.
In case of overdose, get medical help or contact a Poison Control Center right away.

PREGNANCY OR BREAST FEEDING

If pregnant or breastfeeding, ask a health professional before use.

Keep out of reach of children.

OVERDOSAGE

In case of overdose, get medical help or contact a Poison Control Center right away.

Inactive ingredients

Alcohol

Purified water

Directions

Adults: Take ten drops two to three times daily or as recommended by your

health care practitioner.

To be taken 20 minutes away from food.

Place drops directly under the tongue or into 1/4 oz. of water.

Children: Divide dosage by half and follow adult directions.

Indications

Helps promote and maintain normal metabolic functions.

Directions

Adults: Take ten drops two to three times daily or as recommended by your

health care practitioner.

To be taken 20 minutes away from food.

Place drops directly under the tongue or into 1/4 oz. of water.

Children: Divide dosage by half and follow adult directions.

OTHER SAFETY INFORMATION

Tamper-resistant package.

Do not use if outer seal is missing or broken.

Store in a cool, dry place.

PACKAGE LABEL

Genestra Brands

NDC 62106-0744-6

Fucus Complex

HOMEOPATHIC PREPARATION

Helps to promote and maintain
normal metabolic functions.

Contains 90% Alcohol

1.7 fl oz (50 mL)